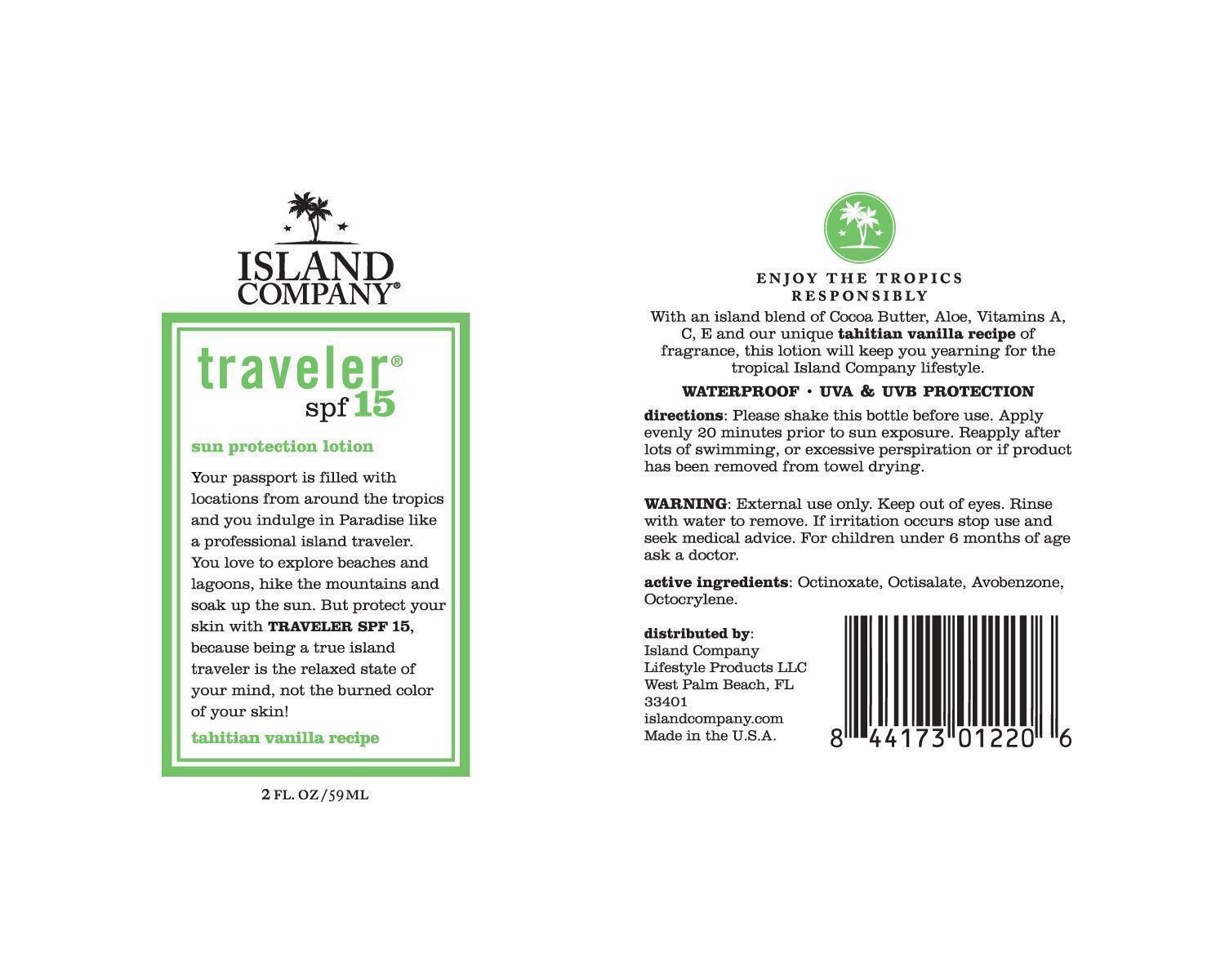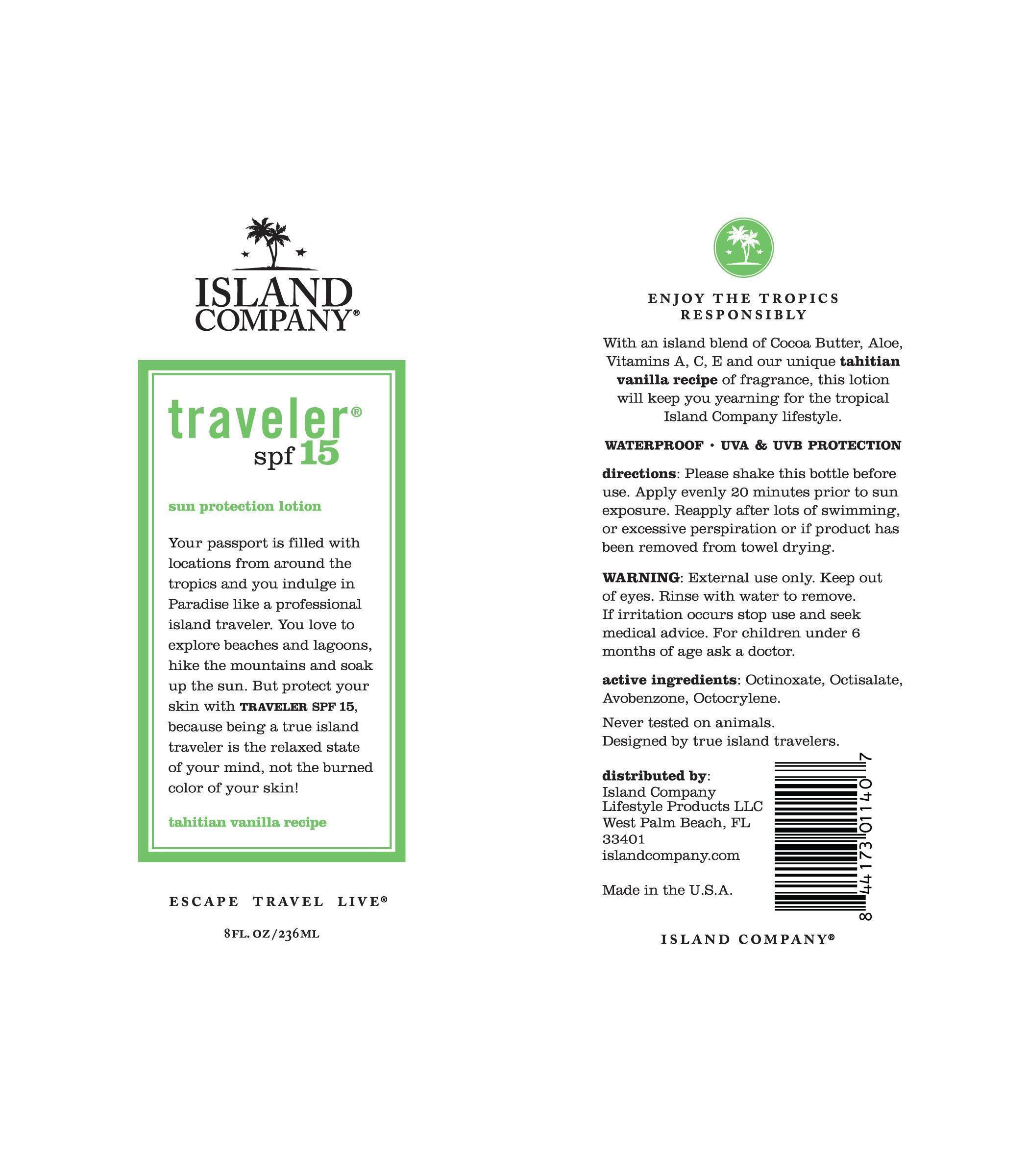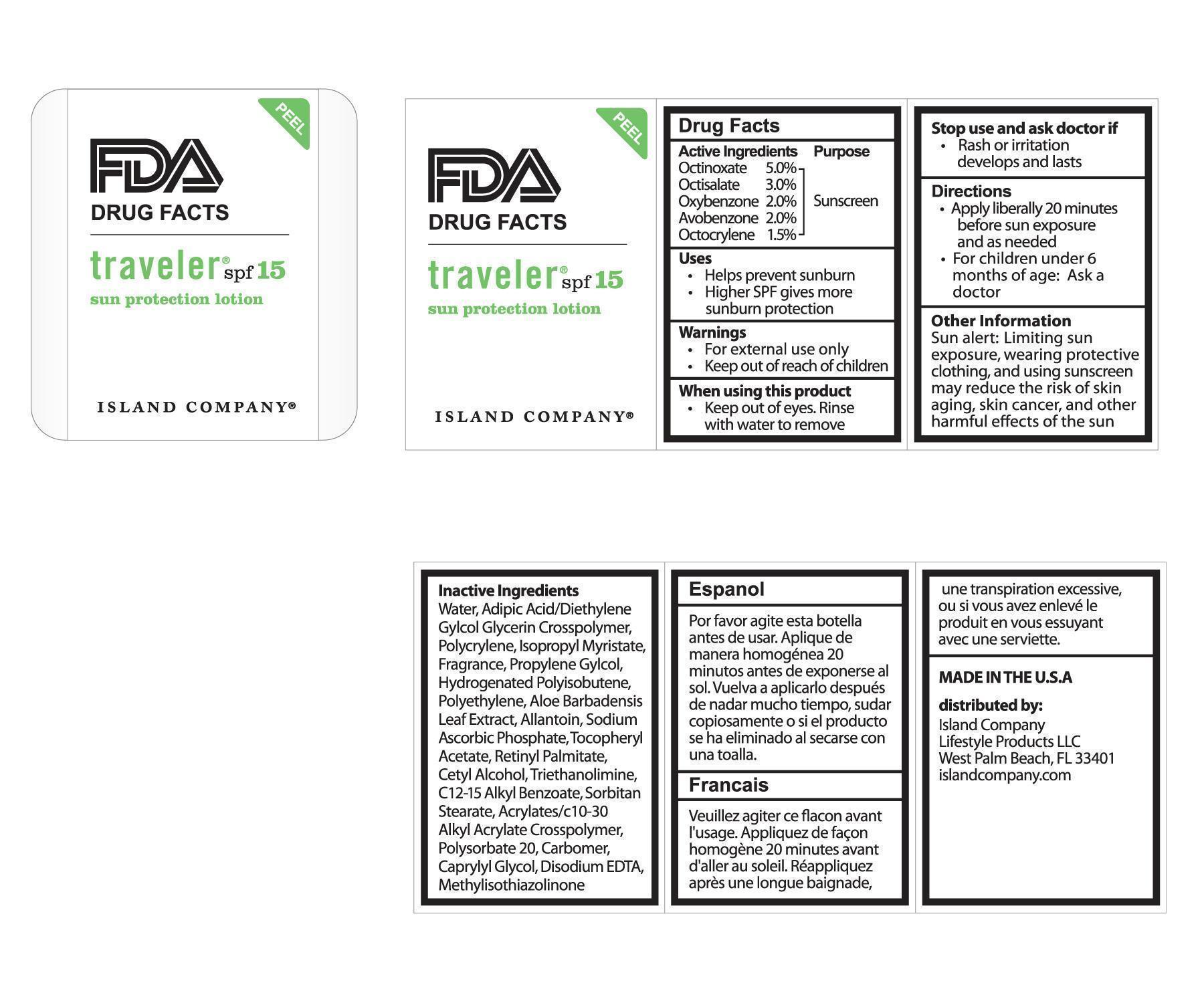 DRUG LABEL: traveler spf15
NDC: 10755-015 | Form: LOTION
Manufacturer: Island Company Lifestyle Products, LLC
Category: otc | Type: HUMAN OTC DRUG LABEL
Date: 20140505

ACTIVE INGREDIENTS: OCTINOXATE 50 mg/1 g; OCTISALATE 30 mg/1 g; AVOBENZONE 20 mg/1 g; OXYBENZONE 20 mg/1 g; OCTOCRYLENE 15 mg/1 g
INACTIVE INGREDIENTS: ADIPIC ACID; DIETHYLENE GLYCOL; GLYCERIN; C12-15 ALKYL BENZOATE; CARBOMER COPOLYMER TYPE A; TROLAMINE; DIPROPYLENE GLYCOL; CAPRYLYL GLYCOL; METHYLISOTHIAZOLINONE; PROPYLENE GLYCOL; ALOE VERA LEAF; ISOPROPYL MYRISTATE; POLYSORBATE 20; HIGH DENSITY POLYETHYLENE; CARBOMER INTERPOLYMER TYPE A (55000 CPS); EDETATE DISODIUM ANHYDROUS; ALLANTOIN; SODIUM ASCORBYL PHOSPHATE; HYDROGENATED POLYBUTENE (1300 MW); CETYL ALCOHOL; POLYESTER-8 (1400 MW, CYANODIPHENYLPROPENOYL CAPPED); .ALPHA.-TOCOPHEROL ACETATE, DL-; VITAMIN A PALMITATE; SORBITAN MONOSTEARATE

traveler spf15

Active Ingredients Purpose

Octinoxate 5.0% Sunscreen

Octisalate 3.0% Sunscreen

Oxybenzone 2.0% Sunscreen

Avobenzone 2.0% Sunscreen

Octocrylene 1.5% Sunscreen

Uses

- Helps prevent sunburn
- Higher SPF gives more sunburn protection

Warnings

- For external use only
- Keep out of reach of children

When using this product

- Keep out of eyes. Rinse with water to remove

Stop use and ask doctor if

- Rash or irritation develops and lasts

Directions

- Apply liberally 20 minutes before sun exposure and as needed
- For children under 6 months of age: Ask a doctor

Other Information

Sun alert: Limiting sun exposure, wearing protective clothing, and using sunscreen may reduce the risk of skin aging, skin cancer, and other harmful effects of the sun

Inactive Ingredients

Water, Adipic Acid/Diethylene Gylcol Glycerin Crosspolymer, Polycrylene, Isopropyl Myristate, Fragrance, Propylene Glycol, Hydrogenated Polyisobutene, Polyethylene, Aloe Barbadensis Leaf Extract, Allantoin, Sodium Ascorbic Phosphate, Tocopheryl Acetate, Retinyl Palmitate, Cetyl Alcohol, Triethanolimine, C12-15 Alkyl Benzoate, Sorbitan Stearate, Acrylates/c10-30 Alkyl Acrylate Crosspolymer, Polysorbate 20, Carbomer, Carpylyl Glycol, Disodium EDTA, Methylisothiazolinone